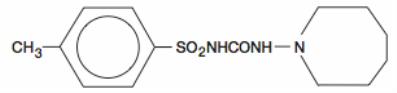 DRUG LABEL: Unknown
Manufacturer: Mutual Pharmaceutical Company, Inc
Category: prescription | Type: Human Prescription Drug Label
Date: 20061228

Rx only

DESCRIPTION

Tolazamide tablets contain tolazamide, an oral blood glucose lowering drug of the sulfonylurea class. Tolazamide is a white or creamy-white powder with a melting point of 165° to 173° C. The solubility of tolazamide at pH 6.0 (mean urinary pH) is 27.8 mg per 100 mL.

The chemical names for tolazamide are (1) Benzenesulfonamide, N-[[(hexahydro-1H-azepin-1-yl) amino] carbonyl]-4-methyl-; (2) 1-(Hexahydro-1H-azepin-1-yl)-3-(p-tolylsulfonyl) urea and its molecular weight is 311.40. The structural formula is represented below:

Tolazamide tablets for oral administration are available as scored, white tablets containing 100 mg, 250 mg or 500 mg tolazamide.

Inactive ingredients: colloidal silicon dioxide, croscarmellose sodium, docusate sodium, magnesium stearate, microcrystalline cellulose, plasdone, sodium benzoate, stearic acid.

CLINICAL PHARMACOLOGY

Actions

Tolazamide appears to lower the blood glucose acutely by stimulating the release of insulin from the pancreas, an effect dependent upon functioning beta cells in the pancreatic islets. The mechanism by which tolazamide lowers blood glucose during long-term administration has not been clearly established. With chronic administration in type II diabetic patients, the blood glucose lowering effect persists despite a gradual decline in the insulin secretory response to the drug. Extrapancreatic effects may be involved in the mechanism of action of oral sulfonylurea hypoglycemic drugs.

Some patients who are initially responsive to oral hypoglycemic drugs, including tolazamide, may become unresponsive or poorly responsive over time. Alternatively, tolazamide may be effective in some patients who have become unresponsive to one or more other sulfonylurea drugs.

In addition to its blood glucose lowering actions, tolazamide produces a mild diuresis by enhancement of renal free water clearance.

Pharmacokinetics

Tolazamide is rapidly and well absorbed from the gastrointestinal tract. Peak serum concentrations occur at three to four hours following a single oral dose of the drug. The average biological half-life of the drug is seven hours. The drug does not continue to accumulate in the blood after the first four to six doses are administered. A steady or equilibrium state is reached during which the peak and nadir values do not change from day to day after the fourth to sixth doses.

Tolazamide is metabolized to five major metabolites ranging in hypoglycemic activity from 0-70%. They are excreted principally in the urine. Following a single oral dose of tritiated tolazamide, 85% of the dose was excreted in the urine and 7% in the feces over a five-day period. Most of the urinary excretion of the drug occurred within the first 24 hours post administration.

When normal fasting nondiabetic subjects are given a single 500 mg dose of tolazamide orally, a hypoglycemic effect can be noted within 20 minutes after ingestion with a peak hypoglycemic effect occurring in two to four hours. Following a single oral dose of 500 mg tolazamide, a statistically significant hypoglycemic effect was demonstrated in fasted nondiabetic subjects 20 hours after administration. With fasting diabetic patients, the peak hypoglycemic effect occurs at four to six hours. The duration of maximal hypoglycemic effect in fed diabetic patients is about ten hours, with the onset occurring at four to six hours and with the blood glucose levels beginning to rise at l4 to16 hours. Single dose potency of tolazamide in normal subjects has been shown to be 6.7 times that of tolbutamide on a milligram basis. Clinical experience in diabetic patients has demonstrated tolazamide to be approximately five times more potent than tolbutamide on a milligram basis, and approximately equivalent in milligram potency to chlorpropamide.

INDICATIONS AND USAGE

Tolazamide tablets are indicated as an adjunct to diet to lower the blood glucose in patients with noninsulin-dependent diabetes mellitus (Type II) whose hyperglycemia cannot be satisfactorily controlled by diet alone.

In initiating treatment for noninsulin-dependent diabetes, diet should be emphasized as the primary form of treatment. Caloric restriction and weight loss are essential in the obese diabetic patient. Proper dietary management alone may be effective in controlling the blood glucose and symptoms of hyperglycemia. The importance of regular physical activity should also be stressed and cardiovascular risk factors should be identified and corrective measures taken where possible.

If this treatment program fails to reduce symptoms and/or blood glucose, the use of an oral sulfonylurea or insulin should be considered. Use of tolazamide must be viewed by both the physician and patient as a treatment in addition to diet and not as a substitute for diet or as a convenient mechanism for avoiding dietary restraint. Furthermore, loss of blood glucose control on diet alone may be transient thus requiring only short-term administration of tolazamide.

During maintenance programs, tolazamide should be discontinued if satisfactory lowering of blood glucose is no longer achieved. Judgments should be based on regular clinical and laboratory evaluations.

In considering the use of tolazamide in asymptomatic patients, it should be recognized that controlling the blood glucose in noninsulin-dependent diabetes has not been definitely established to be effective in preventing the long-term cardiovascular or neural complications of diabetes.

CONTRAINDICATIONS

Tolazamide tablets are contraindicated in patients with: 1) known hypersensitivity or allergy to tolazamide; 2) diabetic ketoacidosis, with or without coma. This condition should be treated with insulin; 3) Type I diabetes, as sole therapy.

SPECIAL WARNING ON INCREASED RISK OF CARDIOVASCULAR MORTALITY

The administration of oral hypoglycemic drugs has been reported to be associated with increased cardiovascular mortality as compared to treatment with diet alone or diet plus insulin. This warning is based on the study conducted by the University Group Diabetes Program (UGDP), a long-term prospective clinical trial designed to evaluate the effectiveness of glucose-lowering drugs in preventing or delaying vascular complications in patients with noninsulin-dependent diabetes. The study involved 823 patients who were randomly assigned to one of four treatment groups (DIABETES, 19 (supp.2):747-830, 1970.)

UGDP reported that patients treated for five to eight years with diet plus a fixed dose of tolbutamide (1.5 grams per day) had a rate of cardiovascular mortality approximately 2½ times that of patients with diet alone. A significant increase in total mortality was not observed, but the use of tolbutamide was discontinued based on the increase in cardiovascular mortality, thus limiting the opportunity for the study to show an increase in overall mortality. Despite controversy regarding the interpretation of these results, the findings of the UGDP study provide an adequate basis for this warning. The patient should be informed of the potential risks and advantages of tolazamide and of alternative modes of therapy.

Although only one drug in the sulfonylurea class (tolbutamide) was included in this study, it is prudent from a safety standpoint to consider that this warning may also apply to other oral hypoglycemic drugs in this class, in view of their close similarities in mode of action and chemical structure.

PRECAUTIONS

General

Hypoglycemia

All sulfonylurea drugs are capable of producing severe hypoglycemia. Proper patient selection and dosage and instructions are important to avoid hypoglycemic episodes. Renal or hepatic insufficiency may cause elevated blood levels of tolazamide and the latter may also diminish gluconeogenic capacity, both of which increase the risk of serious hypoglycemic reactions. Elderly, debilitated, or malnourished patients and those with adrenal or pituitary insufficiency are particularly susceptible to the hypoglycemic action of glucose lowering drugs. Hypoglycemia may be difficult to recognize in the elderly and in people who are taking beta-adrenergic blocking drugs. Hypoglycemia is more likely to occur when caloric intake is deficient, after severe or prolonged exercise, when alcohol is ingested, or when more than one glucose-lowering drug is used.

Loss of Control of Blood Glucose

When a patient stabilized on any diabetic regimen is exposed to stress such as fever, trauma, infection, or surgery, loss of control of blood glucose may occur. At such times it may be necessary to discontinue tolazamide and administer insulin.

The effectiveness of any hypoglycemic drug, including tolazamide, in lowering blood glucose to a desired level decreases in many patients over a period of time, which may be due to progression of the severity of the diabetes or to diminished responsiveness to the drug. This phenomenon is known as secondary failure to distinguish it from primary failure in which the drug is ineffective in an individual patient when first given. Adequate adjustment of dose and adherence to diet should be assessed before classifying a patient as a secondary failure.

Information for Patients

Patients should be informed of the potential risks and advantages of tolazamide and of alternative modes of therapy. They should also be informed about the importance of adherence to dietary instructions, of a regular exercise program, and of regular testing of urine and/or blood glucose.

The risks of hypoglycemia, its symptoms and treatment, and conditions that predispose to its development should be explained to patients and responsible family members. Primary and secondary failure should also be explained.

Laboratory Tests

Blood and urine glucose should be monitored periodically. Measurement of glycosylated hemoglobin may be useful in some patients.

Drug Interactions

The hypoglycemic action of sulfonylureas may be potentiated by certain drugs including nonsteroidal anti-inflammatory agents and other drugs that are highly protein bound, salicylates, sulfonamides, chloramphenicol, probenecid, coumarins, monoamine oxidase inhibitors, and beta-adrenergic blocking agents. When such drugs are administered to a patient receiving tolazamide, the patient should be closely observed for hypoglycemia. When such drugs are withdrawn from a patient receiving tolazamide, the patient should be observed closely for loss of control.

Certain drugs tend to produce hyperglycemia and may lead to loss of control. These drugs include the thiazides and other diuretics, corticosteroids, phenothiazines, thyroid products, estrogens, oral contraceptives, phenytoin, nicotinic acid, sympathomimetics, calcium channel blocking drugs, and isoniazid. When such drugs are administered to a patient receiving tolazamide, the patient should be closely observed for loss of control. When such drugs are withdrawn from a patient receiving tolazamide, the patient should be observed closely for hypoglycemia.

A potential interaction between oral miconazole and oral hypoglycemic agents leading to severe hypoglycemia has been reported. Whether this interaction also occurs with the intravenous, topical or vaginal preparations of miconazole is not known.

Carcinogenicity

In a bioassay for carcinogenicity, rats and mice of both sexes were treated with tolazamide for 103 weeks at low and high doses. No evidence of carcinogenicity was found.

Pregnancy

Teratogenic Effect

Pregnancy Category C

Tolazamide, administered to pregnant rats at ten times the human dose, decreased litter size but did not produce teratogenic effects in the offspring. In rats treated at a daily dose of 14 mg/kg no reproductive aberrations or drug related fetal anomalies were noted. At an elevated dose of 100 mg/kg per day there was a reduction in the number of pups born and an increased perinatal mortality. There are, however, no adequate and well-controlled studies in pregnant women. Because animal reproduction studies are not always predictive of human response, tolazamide is not recommended for the treatment of the pregnant diabetic patient. Serious consideration should also be given to the possible hazards of the use of tolazamide in women of child bearing age and in those who might become pregnant while using the drug.

Because recent information suggests that abnormal blood glucose levels during pregnancy are associated with a higher incidence of congenital abnormalities, many experts recommend that insulin be used during pregnancy to maintain blood glucose levels as close to normal as possible.

Nonteratogenic Effects

Prolonged severe hypoglycemia (four to ten days) has been reported in neonates born to mothers who were receiving a sulfonylurea drug at the time of delivery. This has been reported more frequently with the use of agents with prolonged half-lives. If tolazamide is used during pregnancy, it should be discontinued at least two weeks before the expected delivery date.

Nursing Mothers

Although it is not known whether tolazamide is excreted in human milk, some sulfonylurea drugs are known to be excreted in human milk. Because the potential for hypoglycemia in nursing infants may exist, a decision should be made whether to discontinue nursing or to discontinue the drug, taking into account the importance of the drug to the mother. If the drug is discontinued and if diet alone is inadequate for controlling blood glucose, insulin therapy should be considered.

Pediatric Use

Safety and effectiveness in children have not been established.

Geriatric Use

Elderly patients are particularly susceptible to the hypoglycemic action of glucose lowering drugs. Hypoglycemia may be difficult to recognize in the elderly (see PRECAUTIONS). The initial and maintenance dosing should be conservative to avoid hypoglycemic reactions (see DOSAGE AND ADMINISTRATION).

Elderly patients are prone to develop renal insufficiency, which may put them at risk of hypoglycemia. Dose selection should include assessment of renal function.

ADVERSE REACTIONS

Tolazamide tablets have generally been well tolerated. In clinical studies in which more than 1,784 diabetic patients were specifically evaluated for incidence of side effects, only 2.1% were discontinued from therapy because of side effects.

Hypoglycemia

See PRECAUTIONS and OVERDOSAGE sections.

Gastrointestinal Reactions

Cholestatic jaundice may occur rarely; tolazamide tablets should be discontinued if this occurs. Gastrointestinal disturbances, eg, nausea, epigastric fullness, and heartburn, are the most common reactions and occurred in 1% of patients treated during clinical trials. They tend to be dose-related and may disappear when dosage is reduced.

Dermatologic Reactions

Allergic skin reactions, eg, pruritus, erythema, urticaria, and morbilliform or maculopapular eruptions, occurred in 0.4 % of patients treated during clinical trials. These may be transient and may disappear despite continued use of tolazamide; if skin reactions persist, the drug should be discontinued.

Porphyria cutanea tarda and photosensitivity reactions have been reported with sulfonylureas.

Hematologic Reactions

Leukopenia, agranulocytosis, thrombocytopenia, hemolytic anemia, aplastic anemia, and pancytopenia have been reported with sulfonylureas.

Metabolic Reactions

Hepatic porphyria and disulfiram-like reactions have been reported with sulfonylureas; however, disulfiram-like reactions with tolazamide have been reported very rarely.

Cases of hyponatremia have been reported with tolazamide and all other sulfonylureas, most often in patients who are on other medications or have medical conditions known to cause hyponatremia or increase release of antidiuretic hormone. The syndrome of inappropriate antidiuretic hormone (SIADH) secretion has been reported with certain other sulfonylureas, and it has been suggested that these sulfonylureas may augment the peripheral (antidiuretic) action of ADH and/or increase release of ADH.

Miscellaneous

Weakness, fatigue, dizziness, vertigo, malaise and headache were reported infrequently in patients treated during clinical trials. The relationship to therapy with tolazamide is difficult to assess.

OVERDOSAGE

Overdosage of sulfonylureas, including tolazamide tablets, can produce hypoglycemia.

Mild hypoglycemic symptoms without loss of consciousness or neurologic findings should be treated aggressively with oral glucose and adjustment in drug dosage and/or meal patterns. Close monitoring should continue until the physician is assured the patient is out of danger. Severe hypoglycemic reactions with coma, seizure, or other neurological impairment occur infrequently, but constitute medical emergencies requiring immediate hospitalization. If hypoglycemic coma is suspected or diagnosed, the patient should be given a rapid intravenous injection of concentrated (50%) glucose solution. This should be followed by a continuous infusion of a more dilute (10%) glucose solution at a rate which will maintain the blood glucose at a level above 100 mg/dl. Patients should be closely monitored for a minimum of 24 to 48 hours since hypoglycemia may recur after apparent clinical recovery.

DOSAGE AND ADMINISTRATION

There is no fixed dosage regimen for the management of diabetes mellitus with tolazamide tablets or any other hypoglycemic agent. In addition to the usual monitoring of urinary glucose, the patient’s blood glucose must also be monitored periodically to determine the minimum effective dose for the patient; to detect primary failure, ie, inadequate lowering of blood glucose at the maximum recommended dose of medication; and to detect secondary failure, ie, loss of adequate blood glucose response after an initial period of effectiveness. Glycosylated hemoglobin levels may also be of value in monitoring the patient’s response to therapy.

Short-term administration of tolazamide may be sufficient during periods of transient loss of control in patients usually controlled well on diet.

Usual Starting Dose

The usual starting dose of tolazamide tablets for the mild to moderately severe type II diabetic patient is 100-250 mg daily administered with breakfast or the first main meal. Generally, if the fasting blood glucose is less than 200 mg/dl, the starting dose is 100 mg/day as a single daily dose. If the fasting blood glucose value is greater than 200 mg/dl, the starting dose is 250 mg/day as a single dose. If the patient is malnourished, underweight, elderly, or not eating properly, the initial therapy should be 100 mg once a day. Failure to follow an appropriate dosage regimen may precipitate hypoglycemia. Patients who do not adhere to their prescribed dietary regimen are more prone to exhibit unsatisfactory response to drug therapy.

Transfer From Other Hypoglycemic Therapy

Patients Receiving Other Oral Antidiabetic Therapy

Transfer of patients from other oral antidiabetes regimens to tolazamide should be done conservatively. When transferring patients from oral hypoglycemic agents other than chlorpropamide to tolazamide, no transition period or initial or priming dose is necessary. When transferring from chlorpropamide, particular care should be exercised to avoid hypoglycemia.

Tolbutamide

If receiving less than 1 gm/day, begin at 100 mg of tolazamide per day. If receiving 1 gm or more per day, initiate at 250 mg of tolazamide per day as a single dose.

Chlorpropamide

250 mg of chlorpropamide may be considered to provide approximately the same degree of blood glucose control as 250 mg of tolazamide. The patient should be observed carefully for hypoglycemia during the transition period from chlorpropamide to tolazamide (one to two weeks) due to the prolonged retention of chlorpropamide in the body and the possibility of a subsequent overlapping drug effect.

Acetohexamide

100 mg of tolazamide may be considered to provide approximately the same degree of blood glucose control as 250 mg of acetohexamide.

Patients Receiving Insulin

Some type II diabetic patients who have been treated only with insulin may respond satisfactorily to therapy with tolazamide. If the patient’s previous insulin dosage has been less than 20 units, substitution of 100 mg of tolazamide per day as a single daily dose may be tried. If the previous insulin dosage was less than 40 units, but more than 20 units, the patient should be placed directly on 250 mg of tolazamide per day as a single dose. If the previous insulin dosage was greater than 40 units, the insulin dosage should be decreased by 50% and 250 mg of tolazamide per day started. The dosage of tolazamide should be adjusted weekly (or more often in the group previously requiring more than 40 units of insulin).

During this conversion period when both insulin and tolazamide are being used, hypoglycemia may rarely occur. During insulin withdrawal, patients should test their urine for glucose and acetone at least three times daily and report results to their physician. The appearance of persistent acetonuria with glycosuria indicates that the patient is a Type I diabetic who requires insulin therapy.

Maximum Dose

Daily doses of greater than 1000 mg are not recommended. Patients will generally have no further response to doses larger than this.

Usual Maintenance Dose

The usual maintenance dose is in the range of 100-1000 mg/day with the average maintenance dose being 250-500 mg/day. Following initiation of therapy, dosage adjustment is made in increments of 100 mg to 250 mg at weekly intervals based on the patient’s blood glucose response.

Dosage Interval

Once a day therapy is usually satisfactory. Doses up to 500 mg/day should be given as a single dose in the morning. 500 mg once daily is as effective as 250 mg twice daily. When a dose of more than 500 mg/day is required, the dose may be divided and given twice daily.

In elderly patients, debilitated or malnourished patients, and patients with impaired renal or hepatic function, the initial and maintenance dosing should be conservative to avoid hypoglycemic reactions (see PRECAUTIONS section).

HOW SUPPLIED

TOLAZAMIDE Tablets are supplied as follows:

TOLAZAMIDE Tablets, 100 mg white, round, bisected, debossed MP 68

Bottles of l00 NDC 53489-151-01

Bottles of l000 NDC 53489-151-10

TOLAZAMIDE Tablets, 250 mg white, round, bisected, debossed MP 70

Bottles of l00 NDC 53489-152-01

Bottles of 200 NDC 53489-152-04

Bottles of 500 NDC 53489-152-05

Bottles of 1000 NDC 53489-152-10

TOLAZAMIDE Tablets, 500 mg white, round, bisected, debossed MP 72

Bottles of l00 NDC 53489-153-01

Bottles of 250 NDC 53489-153-03

Bottles of 500 NDC 53489-153-05

Store at 20° to 25°C (68° to 77°F).

[See USP Controlled Room Temperature]

DISPENSE IN TIGHT, LIGHT-RESISTANT CONTAINER.

Manufactured by:

MUTUAL PHARMACEUTICAL COMPANY, INC

Philadelphia, PA 19124 USA

April 2006